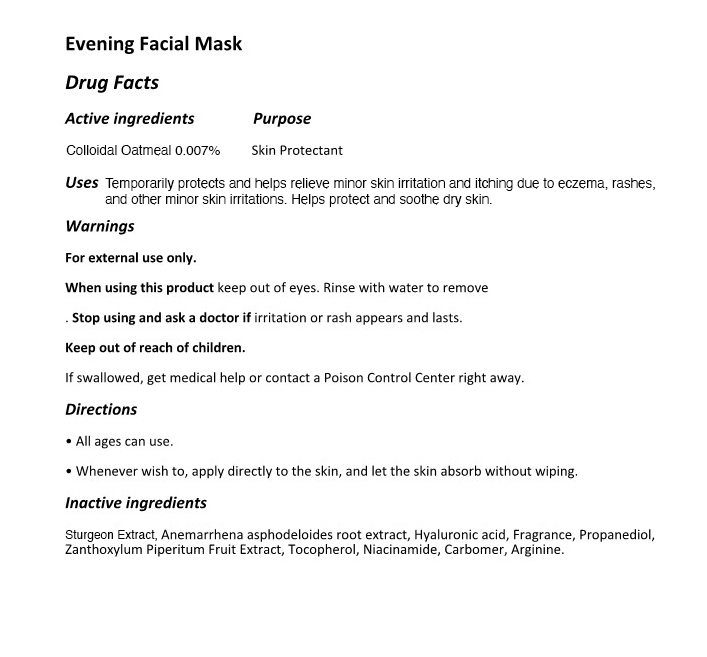 DRUG LABEL: The Zoeun Skin Night Mask
NDC: 83636-117 | Form: LIQUID
Manufacturer: Sturgeonbio Co.,Ltd.
Category: otc | Type: HUMAN OTC DRUG LABEL
Date: 20251001

ACTIVE INGREDIENTS: OATMEAL 0.007 g/100 mL
INACTIVE INGREDIENTS: TOCOPHEROL; PROPANEDIOL; ARGININE; ZANTHOXYLUM PIPERITUM FRUIT PULP; STURGEON, UNSPECIFIED; NIACINAMIDE; CARBOMER HOMOPOLYMER, UNSPECIFIED TYPE; ANEMARRHENA ASPHODELOIDES ROOT; HYALURONIC ACID; FRAGRANCE 13576

117 THE ZOEUN SKIN NIGHT MASK

Active Ingrdients

Colloidal Oatmeal 0.007%

Purpose

Skin Protectant.

Uses

Temporarily protects and helps relieve minor skin irritation and itching due to eczema, rashes, and other minor skin irritations.

Warnings

For external use only.

Warnings

- When using this product keep out of eyes.
- Rinse with water to remove.

Warnings

Stop using and ask a doctor if irritation or rash appears and lasts.

Warnings

- Keep out of reach of children.
- If swallowed, get medical help or contact a Poison Control Center right away.

Directions

- All ages can use.
- Whenever wish to, apply directly to the skin, and let the skin absorb without wiping.

Inactive Ingredients

Surgeon Extract, Anemarrhena asphodeloides root extract, Hyaluronic acid, Fragrance, Propanediol, Zanthoxylum Piperitum Fruit Extract, Tocopherol, Niacinamide, Carbomer, Arginine.